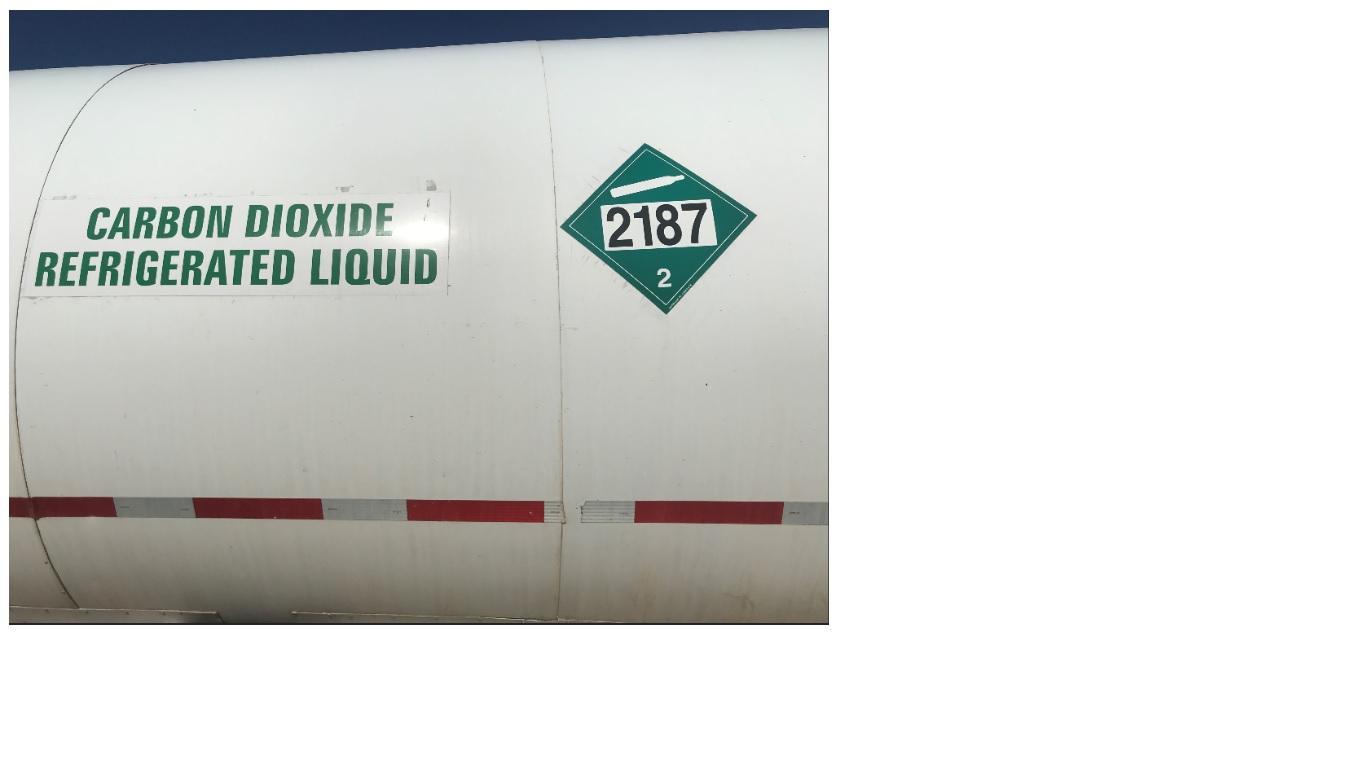 DRUG LABEL: Carbon Dioxide
NDC: 65707-002 | Form: GAS
Manufacturer: Reliant Holdings, Ltd
Category: prescription | Type: HUMAN PRESCRIPTION DRUG LABEL
Date: 20251107

ACTIVE INGREDIENTS: CARBON DIOXIDE 990 mL/1 L

Carbon Dioxide

PACKAGE LABEL

CARBON DIOXIDE REFRIGERATED LIQUID

2187